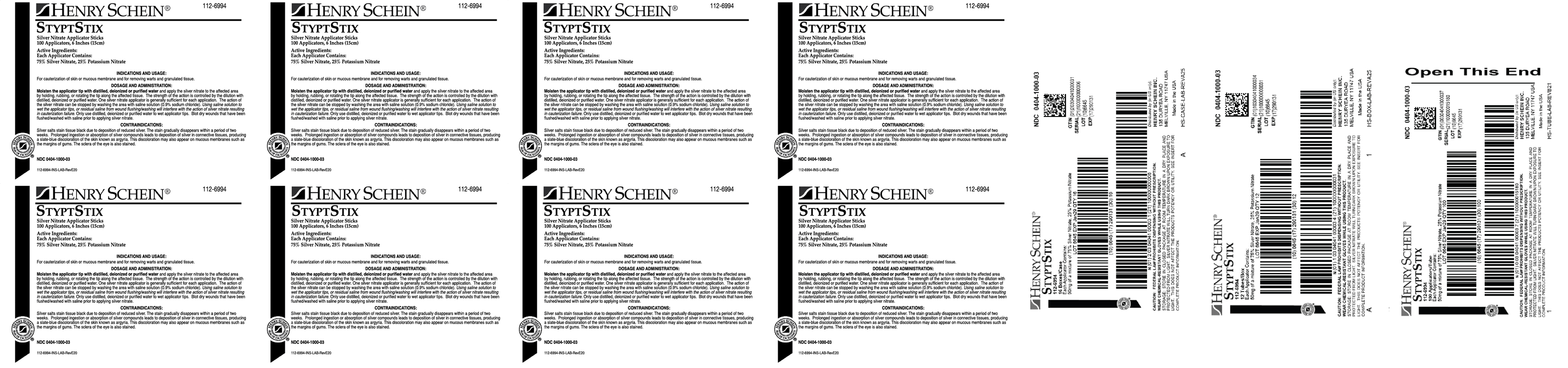 DRUG LABEL: STYPTSTIX
NDC: 0404-1000 | Form: STICK
Manufacturer: Henry Schein Inc.
Category: prescription | Type: HUMAN PRESCRIPTION DRUG LABEL
Date: 20250717

ACTIVE INGREDIENTS: SILVER NITRATE 38.21 mg/1 1; POTASSIUM NITRATE 12.74 mg/1 1
INACTIVE INGREDIENTS: HYDROCHLORIC ACID 0.042 mg/1 1; SODIUM CHLORIDE 0.021 mg/1 1

INDICATIONS AND USAGE:

For cauterization of skin or mucous membrane and for removing warts and granulated tissue.

DOSAGE AND ADMINISTRATION:

Moisten the applicator tip with distilled, deionized or purified water and apply the silver nitrate to the affected area
by holding, rubbing, or rotating the tip along the affected tissue. The strength of the action is controlled by the dilution with
distilled, deionized or purified water. One silver nitrate applicator is generally sufficient for each application. The action of
the silver nitrate can be stopped by washing the area with saline solution (0.9% sodium chloride). Using saline solution to
wet the applicator tips, or residual saline from wound flushing/washing will interfere with the action of silver nitrate resulting
in cauterization failure. Only use distilled, deionized or purified water to wet applicator tips. Blot dry wounds that have been
flushed/washed with saline prior to applying silver nitrate.

DOSAGE FORMS AND STRENGTHS:

Stick: 50 mg

CONTRAINDICATIONS

Silver salts stain tissue black due to deposition of reduced silver. The stain gradually disappears within a period of two
weeks. Prolonged ingestion or absorption of silver compounds leads to deposition of silver in connective tissues, producing
a slate-blue discoloration of the skin known as argyria. This discoloration may also appear on mucous membranes such as
the margins of gums. The sclera of the eye is also stained.

WARNINGS AND PRECAUTIONS:

WARNING: KEEP OUT OF REACH OF CHILDREN. The active ingredients are poisonous and may be fatal when
ingested in sufficient doses. The symptoms include toxic gastroenteritis, which may lead to coma, convulsion,
paralysis and profound alteration of respiration. If poisoning occurs, immediately consult a physician.
WARNING: DO NOT USE ON THE EYES. In case of eye contact, hold eyes open and immediately flush
thoroughly with water for at least 15 minutes and consult a physician.
CAUTION: SILVER NITRATE IS A CAUSTIC SUBSTANCE. Chemical burns may result from inappropriate use of
product.
• Wear chemical resistant gloves while using this product. Wear other appropriate personal protective equipment as
needed.
• Take care to confine the silver nitrate to the area being treated by using an appropriate physical or chemical barrier to
prevent staining or burning of untreated tissue.
• Skin contact time with applicators should be minimal when used on thin delicate skin or neonates.
• Avoid prolonged contact with skin or other surfaces since staining may occur.
CAUTION: FEDERAL LAW PROHIBITS DISPENSING WITHOUT PRESCRIPTION.

STORAGE:

Store in the closed package at room temperature in a dry place protected from light. Silver nitrate will oxidize
and turn dark brown upon exposure to light, however this does not affect the product’s potency or utility.
Exposure to moisture can cause the tip to break or loosen from the applicator. Store away from vaporous
chemicals.

DISPOSAL:

Expired or unused applicators may be disposed of according to applicable federal, state and local regulations.